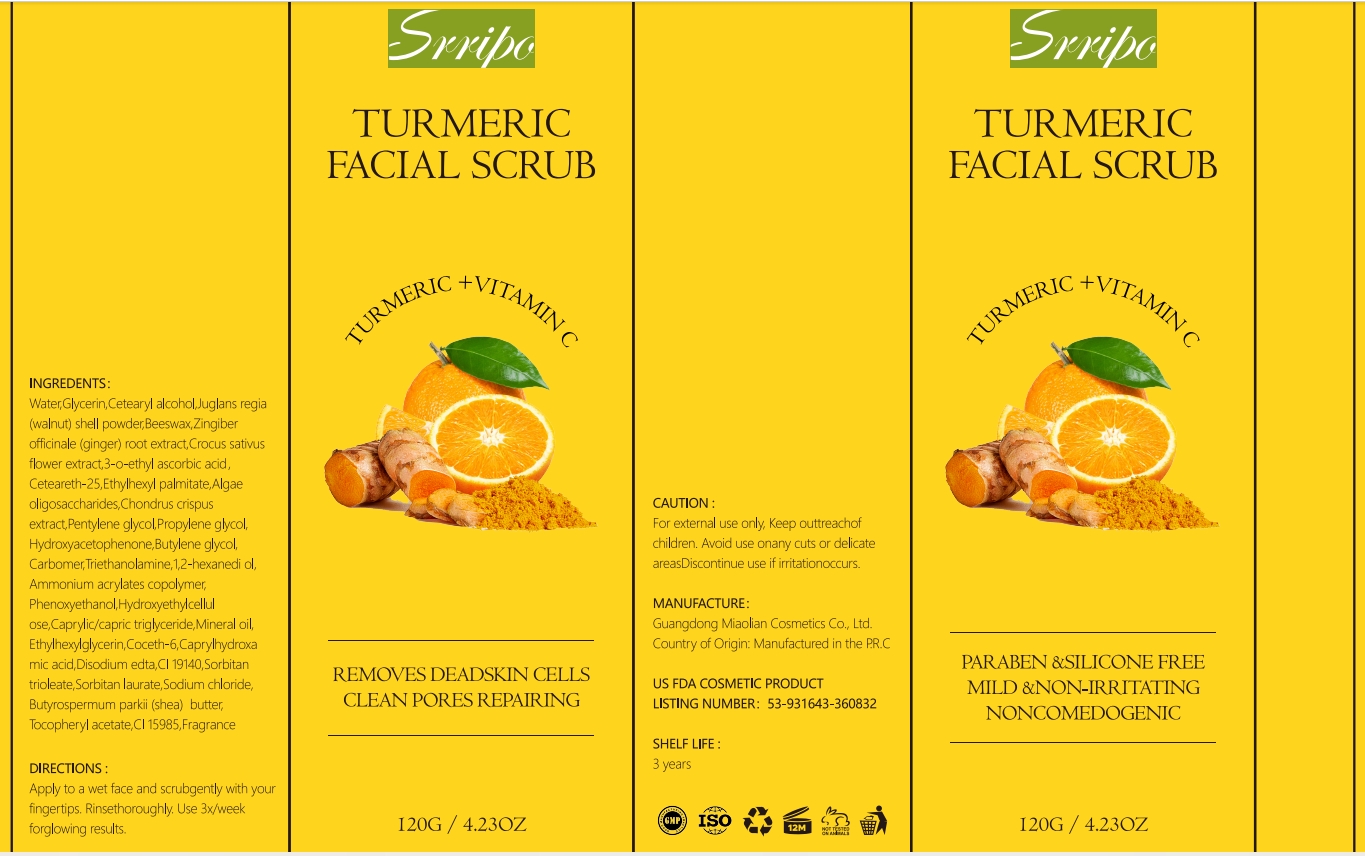 DRUG LABEL: Srripo Turmeric Facial Scrub
NDC: 84507-024 | Form: CREAM
Manufacturer: Guangdong Miaolian Cosmetics Co., Ltd.
Category: otc | Type: HUMAN OTC DRUG LABEL
Date: 20240926

ACTIVE INGREDIENTS: GLYCERIN 4 mg/100 g
INACTIVE INGREDIENTS: JUGLANS REGIA SHELL; CETEARETH-25; ETHYLHEXYL PALMITATE; BUTYLENE GLYCOL; ZINGIBER OFFICINALE WHOLE; PHENOXYETHANOL; ACRYLATES/C10-30 ALKYL ACRYLATE CROSSPOLYMER (60000 MPA.S); CAPRYLIC/CAPRIC/LINOLEIC TRIGLYCERIDE; MINERAL OIL; CETEARETH-6; SORBITAN TRIOLEATE; PROPYLENE GLYCOL; ETHYLHEXYLGLYCERIN; CAPRYLHYDROXAMIC ACID; CROCUS SATIVUS FLOWER; HYDROXYACETOPHENONE; TRIETHYLAMINE; 1,2-HEXANEDIOL; 3-O-ETHYL ASCORBIC ACID; BASIC YELLOW 5; SODIUM CHLORIDE; WATER; CETOSTEARYL ALCOHOL; SHEA BUTTER; PENTYLENE GLYCOL; CHONDRUS CRISPUS; DIRECT YELLOW 6; EDETATE DISODIUM

DOSAGE AND ADMINISTRATION

After using bath fluid, dig out a small amount of scrub cream for the palm, add some water to slowly blend, apply to the whole body

WARNINGS

For external use only

INACTIVE INGREDIENT

WATER
CETEARYL ALCOHOL
JUGLANS REGIA (WALNUT) SHELL POWDER
BEESWAX
CETEARETH-25
ETHYLHEXYL PALMITATE
BUTYLENE GLYCOL
ZINGIBER OFFICINALE (GINGER) ROOT EXTRACT
PHENOXYETHANOL
AMMONIUM ACRYLATES COPOLYMER
CAPRYLIC/CAPRIC TRIGLYCERIDE
MINERAL OIL
COCETH-6
SORBITAN TRIOLEATE
PROPYLENE GLYCOL
ETHYLHEXYLGLYCERIN
CAPRYLHYDROXAMIC ACID
CROCUS SATIVUS FLOWER EXTRACT
HYDROXYACETOPHENONE
CARBOMER
TRIETHANOLAMINE
1,2-HEXANEDIOL
FRAGRANCE
3-o-ETHYL ASCORBIC ACID
CI 19140
SODIUM CHLORIDE
CI 15985
DISODIUM EDTA
BUTYROSPERMUM PARKII (SHEA) BUTTER
PENTYLENE GLYCOL
CHONDRUS CRISPUS EXTRACT

INDICATIONS AND USAGE

Body Horny thick

keep out of chlidren

PURPOSE

Gentle exfoliationImprove skin condition Moisturize skin

ACTIVE INGREDIENT

GLYCERIN